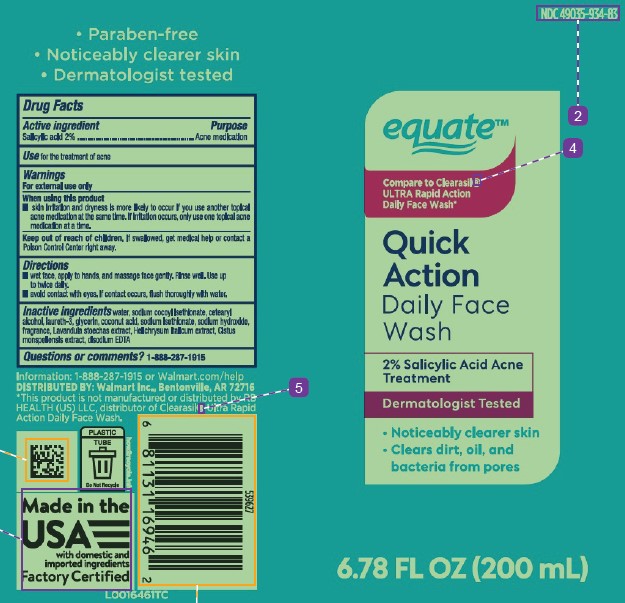 DRUG LABEL: Quick Action
NDC: 49035-934 | Form: LIQUID
Manufacturer: Walmart Inc.
Category: otc | Type: HUMAN OTC DRUG LABEL
Date: 20260227

ACTIVE INGREDIENTS: SALICYLIC ACID 2 g/100 mL
INACTIVE INGREDIENTS: WATER; SODIUM COCOYL ISETHIONATE; CETOSTEARYL ALCOHOL; LAURETH-3; GLYCERIN; COCONUT ACID; SODIUM ISETHIONATE; SODIUM HYDROXIDE; LAVANDULA ANGUSTIFOLIA FLOWERING TOP; HELICHRYSUM ITALICUM FLOWER; CISTUS MONSPELIENSIS WHOLE; EDETATE DISODIUM ANHYDROUS

Equate 580.000/580AA
Quick Action Daily Face Wash

Claims

- Paraben-free
- Noticeably clearer skin
- Dermatologist tested

Active ingredient

Salicylic acid 2%

Purpose

Acne medication

Use

for the treatment of acne

Warnings

For external use only

When using this product

- skin irritation and dryness is more likely to occur if you use another topical acne medication at the same time. If irritation occurs, only use one topical acne medication at a time.

Keep out of reach of children.

If swallowed, get medical help or contact a Poison Control Center right away.

Directions

- wet face, apply to hand, massage face gently. Rinse well. Use up to twice daily.
- avoid contact with eyes. If contact occurs, flush thoroughly with water.

Inactive ingredients

water, sodium cocoyl isethionate, cetearyl alcohol, laureth-3, glycerin, coconut acid, sodium isethionate, sodium hydroxide, fragrance, Lavandula stoechas extract, Helichrysum italicum extract, Cistus monspeliensis extract, disodium EDTA

Questions or comments?

1-888-287-1915

Disclaimer

*This product is not manufactured or distributed by RB HEALTH (US) LLC, distributor of Clearasil®Ultra Rapid Action Daily Face Wash.

ADVERSE REACTION

Information: 1-888-287-1915 or Walmart.com/help

DISTRIBUTED BY: Walmart Inc., Bentonville, AR 72716

PLASTIC TUBE

Do Not Recycle

how2recycle.info

Made in the USA with domestic and imported ingredients.

Factory Certified

principal display panel

NDC 49035-934-83

equate™

COMPARE TO CLEARASIL® ULTRA RAPID ACTION DAILY FACE WASH*

QUICK ACTION

DAILY FACE WASH

2% Salicylic Acid Acne Treatment

Dermatologist Tested

- Noticeably clearer skin
- Clears dirt, oil and bacteria from pores

6.78 FL OZ (200 mL)